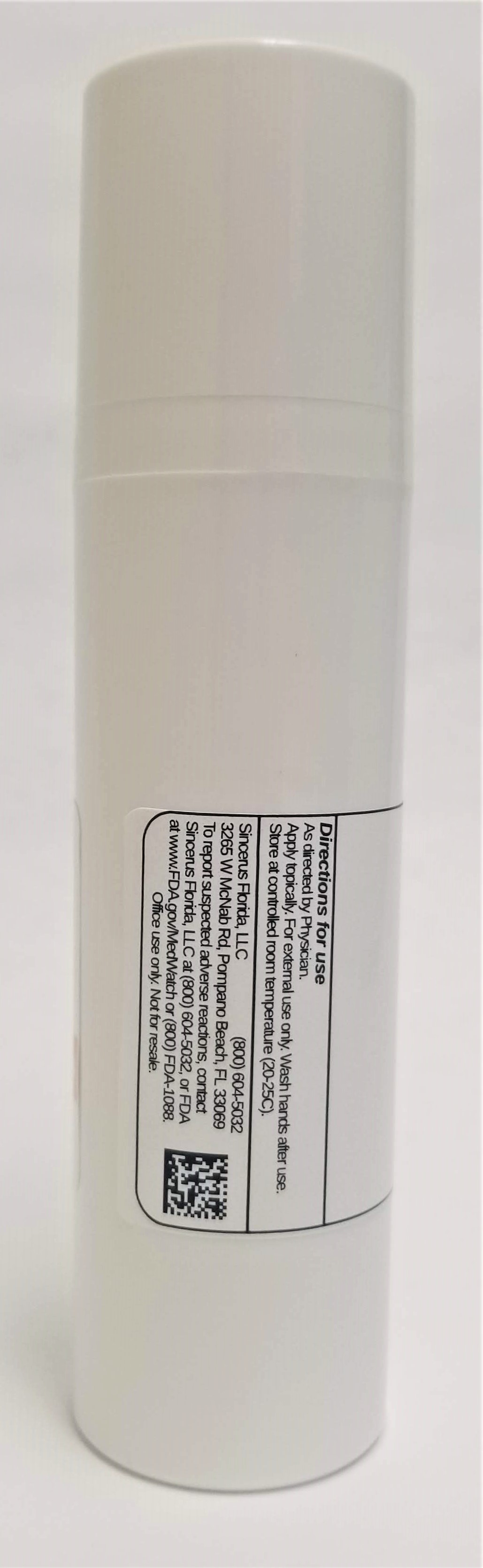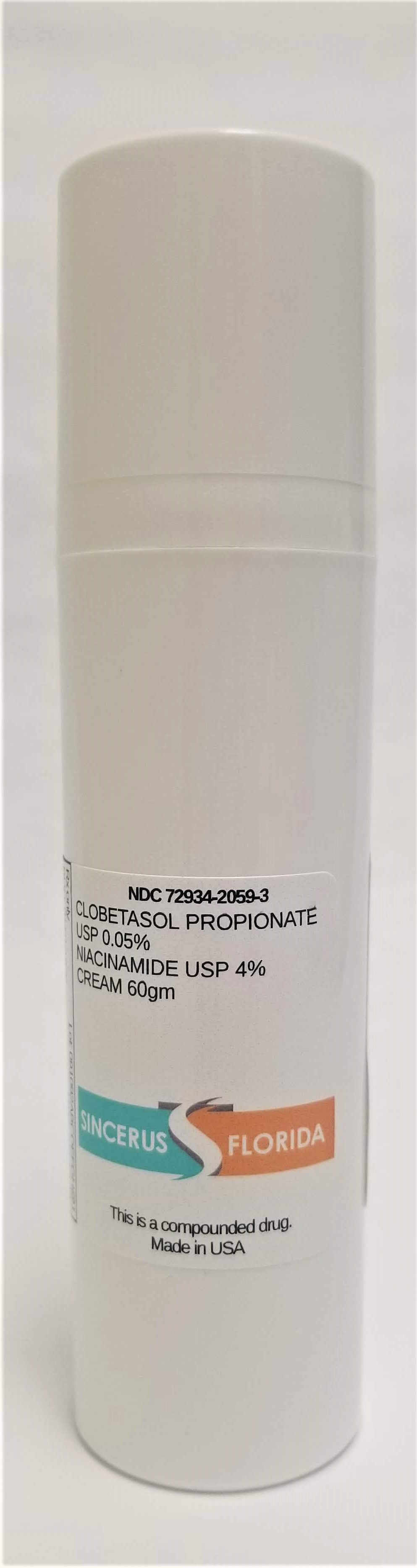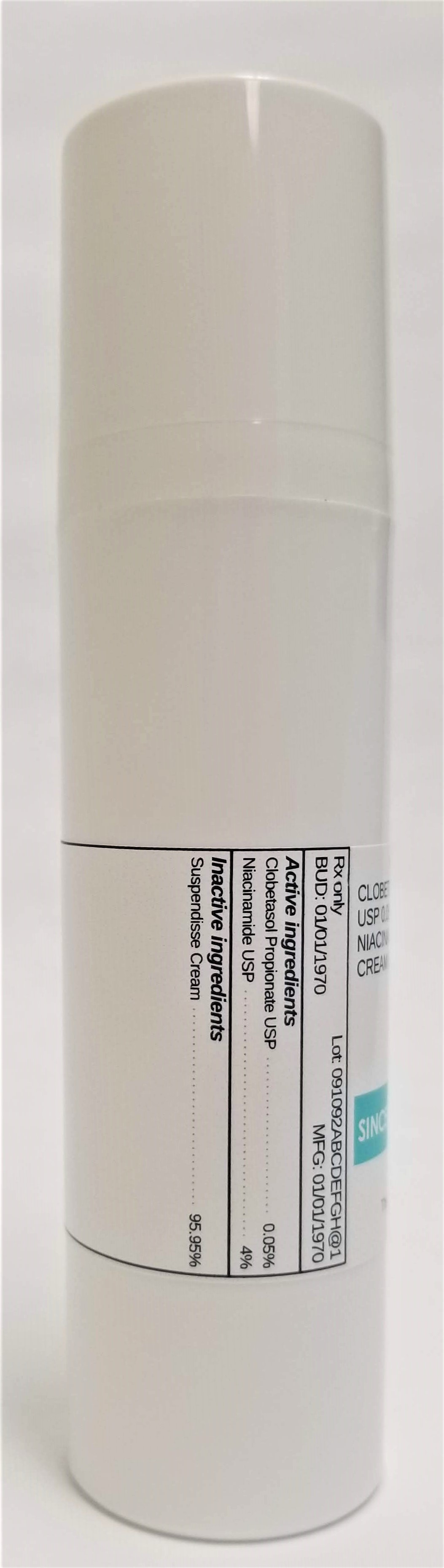 DRUG LABEL: CLOBETASOL PROPIONATE 0.05% / NIACINAMIDE 4%
NDC: 72934-2059 | Form: CREAM
Manufacturer: Sincerus Florida, LLC
Category: prescription | Type: HUMAN PRESCRIPTION DRUG LABEL
Date: 20190430

ACTIVE INGREDIENTS: CLOBETASOL PROPIONATE 0.05 g/100 g; NIACINAMIDE 4 g/100 g

CLOBETASOL PROPIONATE 0.05% / NIACINAMIDE 4%